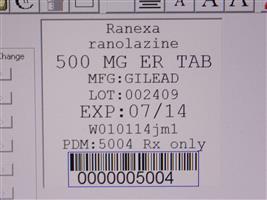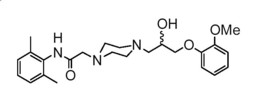 DRUG LABEL: Ranexa
NDC: 68151-5004 | Form: TABLET, FILM COATED, EXTENDED RELEASE
Manufacturer: Carilion Materials Management
Category: prescription | Type: HUMAN PRESCRIPTION DRUG LABEL
Date: 20160806

ACTIVE INGREDIENTS: RANOLAZINE 500 mg/1 1
INACTIVE INGREDIENTS: CARNAUBA WAX; HYPROMELLOSES; MAGNESIUM STEARATE; METHACRYLIC ACID - ETHYL ACRYLATE COPOLYMER (1:1) TYPE A; CELLULOSE, MICROCRYSTALLINE; SODIUM HYDROXIDE; POLYVINYL ALCOHOL; TITANIUM DIOXIDE; POLYETHYLENE GLYCOL 3350; TALC; FERRIC OXIDE YELLOW; FERRIC OXIDE RED; WATER

HIGHLIGHTS OF PRESCRIBING INFORMATION

These highlights do not include all the information needed to use RANEXA safely and effectively. See full prescribing information for RANEXA.
RANEXA ® (ranolazine) extended-release tablets, for oral use
Initial U.S. Approval: 2006

1 INDICATIONS AND USAGE

RANEXA is an antianginal indicated for the treatment of chronic angina. (1)

2 DOSAGE AND ADMINISTRATION

- 500 mg twice daily and increase to 1000 mg twice daily, based on clinical symptoms (2.1)

3 DOSAGE FORMS AND STRENGTHS

Extended-release tablets: 500 mg, 1000 mg (3)

4 CONTRAINDICATIONS

- Strong CYP3A inhibitors (e.g., ketoconazole, clarithromycin, nelfinavir) (4, 7.1)
- CYP3A inducers (e.g., rifampin, phenobarbital, St. John's wort) (4, 7.1)
- Liver cirrhosis (4, 8.6)

5 WARNINGS AND PRECAUTIONS

- QT interval prolongation: Can occur with ranolazine. Little data available on high doses, long exposure, use with QT interval-prolonging drugs, potassium channel variants causing prolonged QT interval, in patients with a family history of (or congenital) long QT syndrome, or in patients with known acquired QT interval prolongation. (5.1)
- Renal failure: Monitor renal function after initiation and periodically in patients with moderate to severe renal impairment (CrCL<60 mL/min). If acute renal failure develops, discontinue RANEXA. (5.2)

6 ADVERSE REACTIONS

Most common adverse reactions (> 4% and more common than with placebo) are dizziness, headache, constipation, nausea. (6.1)

To report SUSPECTED ADVERSE REACTIONS, contact Gilead Sciences, Inc., at 1-800-GILEAD-5 or FDA at 1-800-FDA-1088 or www.fda.gov/medwatch.

7 DRUG INTERACTIONS

- Moderate CYP3A inhibitors (e.g., diltiazem, verapamil, erythromycin): Limit RANEXA to 500 mg twice daily. (7.1)
- P-gp inhibitors (e.g., cyclosporine): Ranolazine exposure increased. Titrate RANEXA based on clinical response. (7.1)
- CYP3A substrates: Limit simvastatin to 20 mg when used with RANEXA. Doses of other sensitive CYP3A substrates (e.g., lovastatin) and CYP3A substrates with narrow therapeutic range (e.g., cyclosporine, tacrolimus, sirolimus) may need to be reduced with RANEXA. (7.2)
- OCT2 substrates: Limit the dose of metformin to 1700 mg daily when used with RANEXA 1000 mg twice daily. Doses of other OCT2 substrates may require adjusted doses. (7.2)
- Drugs transported by P-gp (e.g., digoxin), or drugs metabolized by CYP2D6 (e.g., tricyclic antidepressants) may need reduced doses when used with RANEXA. (7.2)

FULL PRESCRIBING INFORMATION

1 INDICATIONS AND USAGE

RANEXA® is indicated for the treatment of chronic angina.

RANEXA may be used with beta-blockers, nitrates, calcium channel blockers, anti-platelet therapy, lipid-lowering therapy, ACE inhibitors, and angiotensin receptor blockers.

2 DOSAGE AND ADMINISTRATION

2.1 Dosing Information

Initiate RANEXA dosing at 500 mg twice daily and increase to 1000 mg twice daily, as needed, based on clinical symptoms. Take RANEXA with or without meals. Swallow RANEXA tablets whole; do not crush, break, or chew.

The maximum recommended daily dose of RANEXA is 1000 mg twice daily.

If a dose of RANEXA is missed, take the prescribed dose at the next scheduled time; do not double the next dose.

2.2 Dose Modification

Dose adjustments may be needed when RANEXA is taken in combination with certain other drugs [see Drug Interactions (7.1)]. Limit the maximum dose of RANEXA to 500 mg twice daily in patients on moderate CYP3A inhibitors such as diltiazem, verapamil, and erythromycin. Use of RANEXA with strong CYP3A inhibitors is contraindicated [see Contraindications (4), Drug Interactions (7.1)]. Use of P-gp inhibitors, such as cyclosporine, may increase exposure to RANEXA. Titrate RANEXA based on clinical response [see Drug Interactions (7.1)].

3 DOSAGE FORMS AND STRENGTHS

RANEXA is supplied as film-coated, oblong-shaped, extended-release tablets in the following strengths:

- 500 mg tablets are light orange, with GSI500 on one side
- 1000 mg tablets are pale yellow, with GSI1000 on one side

4 CONTRAINDICATIONS

RANEXA is contraindicated in patients:

- Taking strong inhibitors of CYP3A [see Drug Interactions (7.1)]
- Taking inducers of CYP3A [see Drug Interactions (7.1)]
- With liver cirrhosis [see Use in Specific Populations (8.6)]

5 WARNINGS AND PRECAUTIONS

5.1 QT Interval Prolongation

Ranolazine blocks IKr and prolongs the QTc interval in a dose-related manner.

Clinical experience in an acute coronary syndrome population did not show an increased risk of proarrhythmia or sudden death [see Clinical Studies (14.2)]. However, there is little experience with high doses (> 1000 mg twice daily) or exposure, other QT-prolonging drugs, potassium channel variants resulting in a long QT interval, in patients with a family history of (or congenital) long QT syndrome, or in patients with known acquired QT interval prolongation.

5.2 Renal Failure

Acute renal failure has been observed in some patients with severe renal impairment (creatinine clearance [CrCL] < 30 mL/min) while taking RANEXA. If acute renal failure develops (e.g., marked increase in serum creatinine associated with an increase in blood urea nitrogen [BUN]), discontinue RANEXA and treat appropriately [see Use in Specific Populations (8.7)].

Monitor renal function after initiation and periodically in patients with moderate to severe renal impairment (CrCL < 60 mL/min) for increases in serum creatinine accompanied by an increase in BUN.

6 ADVERSE REACTIONS

6.1 Clinical Trial Experience

Because clinical trials are conducted under widely varying conditions, adverse reaction rates observed in the clinical trials of a drug cannot be directly compared to rates in the clinical trials of another drug and may not reflect the rates observed in practice.

A total of 2018 patients with chronic angina were treated with ranolazine in controlled clinical trials. Of the patients treated with RANEXA, 1026 were enrolled in three double-blind, placebo-controlled, randomized studies (CARISA, ERICA, MARISA) of up to 12 weeks' duration. In addition, upon study completion, 1251 patients received treatment with RANEXA in open-label, long-term studies; 1227 patients were exposed to RANEXA for more than 1 year, 613 patients for more than 2 years, 531 patients for more than 3 years, and 326 patients for more than 4 years.

At recommended doses, about 6% of patients discontinued treatment with RANEXA because of an adverse event in controlled studies in angina patients compared to about 3% on placebo. The most common adverse events that led to discontinuation more frequently on RANEXA than placebo were dizziness (1.3% versus 0.1%), nausea (1% versus 0%), asthenia, constipation, and headache (each about 0.5% versus 0%). Doses above 1000 mg twice daily are poorly tolerated.

In controlled clinical trials of angina patients, the most frequently reported treatment-emergent adverse reactions (> 4% and more common on RANEXA than on placebo) were dizziness (6.2%), headache (5.5%), constipation (4.5%), and nausea (4.4%). Dizziness may be dose-related. In open-label, long-term treatment studies, a similar adverse reaction profile was observed.

The following additional adverse reactions occurred at an incidence of 0.5 to 4.0% in patients treated with RANEXA and were more frequent than the incidence observed in placebo-treated patients:

Cardiac Disorders – bradycardia, palpitations

Ear and Labyrinth Disorders – tinnitus, vertigo

Eye Disorders – blurred vision

Gastrointestinal Disorders – abdominal pain, dry mouth, vomiting, dyspepsia

General Disorders and Administrative Site Adverse Events – asthenia, peripheral edema

Metabolism and Nutrition Disorders – anorexia

Nervous System Disorders – syncope (vasovagal)

Psychiatric Disorders – confusional state

Renal and Urinary Disorders – hematuria

Respiratory, Thoracic, and Mediastinal Disorders – dyspnea

Skin and Subcutaneous Tissue Disorders – hyperhidrosis

Vascular Disorders – hypotension, orthostatic hypotension

Other (< 0.5%) but potentially medically important adverse reactions observed more frequently with RANEXA than placebo treatment in all controlled studies included: angioedema, renal failure, eosinophilia, chromaturia, blood urea increased, hypoesthesia, paresthesia, tremor, pulmonary fibrosis, thrombocytopenia, leukopenia, and pancytopenia.

A large clinical trial in acute coronary syndrome patients was unsuccessful in demonstrating a benefit for RANEXA, but there was no apparent proarrhythmic effect in these high-risk patients [see Clinical Studies (14.2)].

Laboratory Abnormalities:

RANEXA produces elevations of serum creatinine by 0.1 mg/dL, regardless of previous renal function, likely because of inhibition of creatinine's tubular secretion. In general, the elevation has a rapid onset, shows no signs of progression during long-term therapy, is reversible after discontinuation of RANEXA, and is not accompanied by changes in BUN. In healthy volunteers, RANEXA 1000 mg twice daily had no effect upon the glomerular filtration rate. More marked and progressive increases in serum creatinine, associated with increases in BUN or potassium, indicating acute renal failure, have been reported after initiation of RANEXA in patients with severe renal impairment [see Warnings and Precautions (5.2), Use in Specific Populations (8.7)].

6.2 Postmarketing Experience

The following adverse reactions have been identified during postapproval use of RANEXA. Because these reactions are reported voluntarily from a population of uncertain size, it is not always possible to reliably estimate their frequency or establish a causal relationship to drug exposure:

Nervous System Disorders – Tremor, paresthesia, abnormal coordination, and other serious neurologic adverse events have been reported to occur, sometimes concurrently, in patients taking ranolazine. The onset of events was often associated with an increase in ranolazine dose or exposure. Many patients reported symptom resolution following drug discontinuation or dose decrease.

Metabolism and Nutrition Disorders – Cases of hypoglycemia have been reported in diabetic patients on antidiabetic medication.

Psychiatric Disorders – hallucination

Renal and Urinary Disorders – dysuria, urinary retention

Skin and Subcutaneous Tissue Disorders – angioedema, pruritus, rash

7 DRUG INTERACTIONS

7.1 Effects of Other Drugs on Ranolazine

Strong CYP3A Inhibitors

Do not use RANEXA with strong CYP3A inhibitors, including ketoconazole, itraconazole, clarithromycin, nefazodone, nelfinavir, ritonavir, indinavir, and saquinavir [see Contraindications (4), Clinical Pharmacology (12.3)].

Moderate CYP3A Inhibitors

Limit the dose of RANEXA to 500 mg twice daily in patients on moderate CYP3A inhibitors, including diltiazem, verapamil, erythromycin, fluconazole, and grapefruit juice or grapefruit-containing products [see Dosage and Administration (2.2), Clinical Pharmacology (12.3)].

P-gp Inhibitors

Concomitant use of RANEXA and P-gp inhibitors, such as cyclosporine, may result in increases in ranolazine concentrations. Titrate RANEXA based on clinical response in patients concomitantly treated with predominant P-gp inhibitors such as cyclosporine [see Dosage and Administration (2.2)].

CYP3A Inducers

Do not use RANEXA with CYP3A inducers such as rifampin, rifabutin, rifapentine, phenobarbital, phenytoin, carbamazepine, and St. John's wort [see Contraindications (4), Clinical Pharmacology (12.3)].

7.2 Effects of Ranolazine on Other Drugs

Drugs Metabolized by CYP3A

Limit the dose of simvastatin in patients on any dose of RANEXA to 20 mg once daily, when ranolazine is co-administered. Dose adjustment of other sensitive CYP3A substrates (e.g., lovastatin) and CYP3A substrates with a narrow therapeutic range (e.g., cyclosporine, tacrolimus, sirolimus) may be required as RANEXA may increase plasma concentrations of these drugs [see Clinical Pharmacology (12.3)].

Drugs Transported by P-gp

Concomitant use of ranolazine and digoxin results in increased exposure to digoxin. The dose of digoxin may have to be adjusted [see Clinical Pharmacology (12.3)].

Drugs Metabolized by CYP2D6

The exposure to CYP2D6 substrates, such as tricyclic antidepressants and antipsychotics, may be increased during co-administration with RANEXA, and lower doses of these drugs may be required.

Drugs Transported by OCT2

In subjects with type 2 diabetes mellitus, concomitant use of RANEXA 1000 mg twice daily and metformin results in increased plasma levels of metformin. When RANEXA 1000 mg twice daily is co-administered with metformin, metformin dose should not exceed 1700 mg/day. Monitor blood glucose levels and risks associated with high exposures of metformin. Metformin exposure was not significantly increased when given with RANEXA 500 mg twice daily [see Clinical Pharmacology (12.3)].

8 USE IN SPECIFIC POPULATIONS

8.1 Pregnancy

Risk Summary

There are no available data on RANEXA use in pregnant women to inform any drug-associated risks. Studies in rats and rabbits showed no evidence of fetal harm at exposures 4 times the maximum recommended human dose (MRHD) (see Data).

In the U.S. general population, the estimated background risk of major birth defects and of miscarriage of clinically recognized pregnancies is 2–4% and 15–20%, respectively.

Data

Animal Data

Embryofetal toxicity studies were conducted in rats and rabbits orally administered ranolazine during organogenesis. In rats, decreased fetal weight and reduced ossification were observed at doses (corresponding to 4-fold the AUC for the MRHD) that caused maternal weight loss. No adverse fetal effects were observed in either species exposed (AUC) to ranolazine at exposures (AUC) equal to the MRHD.

8.2 Lactation

Risk Summary

There are no data on the presence of ranolazine in human milk, the effects on the breastfed infant, or the effects on milk production. However, ranolazine is present in rat milk [see Use in Specific Populations (8.1)]. The developmental and health benefits of breastfeeding should be considered along with the mother's clinical need for RANEXA and any potential adverse effects on the breastfed infant from RANEXA or from the underlying maternal condition.

Adult female rats were administered ranolazine orally from gestation day 6 through postnatal day 20. No adverse effects on pup development, behavior, or reproduction parameters were observed at a maternal dosage level of 60 mg/kg/day (equal to the MHRD based on AUC). At maternally toxic doses, male and female pups exhibited increased mortality and decreased body weight, and female pups showed increased motor activity. The pups were potentially exposed to low amounts of ranolazine via the maternal milk.

8.4 Pediatric Use

Safety and effectiveness have not been established in pediatric patients.

8.5 Geriatric Use

Of the chronic angina patients treated with RANEXA in controlled studies, 496 (48%) were ≥ 65 years of age, and 114 (11%) were ≥ 75 years of age. No overall differences in efficacy were observed between older and younger patients. There were no differences in safety for patients ≥ 65 years compared to younger patients, but patients ≥ 75 years of age on RANEXA, compared to placebo, had a higher incidence of adverse events, serious adverse events, and drug discontinuations due to adverse events. In general, dose selection for an elderly patient should usually start at the low end of the dosing range, reflecting the greater frequency of decreased hepatic, renal, or cardiac function, and of concomitant disease, or other drug therapy.

8.6 Use in Patients with Hepatic Impairment

RANEXA is contraindicated in patients with liver cirrhosis. In a study of cirrhotic patients, the Cmax of ranolazine was increased 30% in cirrhotic patients with mild (Child-Pugh Class A) hepatic impairment, but increased 80% in cirrhotic patients with moderate (Child-Pugh Class B) hepatic impairment compared to patients without hepatic impairment. This increase was not enough to account for the 3-fold increase in QT prolongation seen in cirrhotic patients with mild to moderate hepatic impairment [see Clinical Pharmacology (12.2)].

8.7 Use in Patients with Renal Impairment

A pharmacokinetic study of RANEXA in subjects with severe renal impairment (CrCL < 30 mL/min) was stopped when 2 of 4 subjects developed acute renal failure after receiving RANEXA 500 mg twice daily for 5 days (lead-in phase) followed by 1000 mg twice a day (1 dose in one subject and 11 doses in the other). Increases in creatinine, BUN, and potassium were observed in 3 subjects during the 500 mg lead-in phase. One subject required hemodialysis, while the other 2 subjects improved upon drug discontinuation [see Warnings and Precautions (5.2)]. Monitor renal function periodically in patients with moderate to severe renal impairment. Discontinue RANEXA if acute renal failure develops.

In a separate study, Cmax was increased between 40% and 50% in patients with mild, moderate, or severe renal impairment compared to patients with no renal impairment, suggesting a similar increase in exposure in patients with renal failure independent of the degree of impairment. The pharmacokinetics of ranolazine has not been assessed in patients on dialysis.

8.8 Use in Patients with Heart Failure

Heart failure (NYHA Class I to IV) had no significant effect on ranolazine pharmacokinetics. RANEXA had minimal effects on heart rate and blood pressure in patients with angina and heart failure NYHA Class I to IV. No dose adjustment of RANEXA is required in patients with heart failure.

8.9 Use in Patients with Diabetes Mellitus

A population pharmacokinetic evaluation of data from angina patients and healthy subjects showed no effect of diabetes on ranolazine pharmacokinetics. No dose adjustment is required in patients with diabetes.

RANEXA produces small reductions in HbA1c in patients with diabetes, the clinical significance of which is unknown. RANEXA should not be considered a treatment for diabetes.

10 OVERDOSAGE

High oral doses of ranolazine produce dose-related increases in dizziness, nausea, and vomiting. High intravenous exposure also produces diplopia, paresthesia, confusion, and syncope. In addition to general supportive measures, continuous ECG monitoring may be warranted in the event of overdose. Severe tremor, unsteady gait/incoordination, dysphasia, and hallucinations have been reported in cases of overdose with RANEXA.

Since ranolazine is about 62% bound to plasma proteins, hemodialysis is unlikely to be effective in clearing ranolazine.

11 DESCRIPTION

RANEXA (ranolazine) is available as a film-coated, non-scored, extended-release tablet for oral administration.

Ranolazine is a racemic mixture, chemically described as 1-piperazineacetamide, N-(2,6-dimethylphenyl)-4-[2-hydroxy-3-(2-methoxyphenoxy)propyl]-, (±)-. It has an empirical formula of C24H33N3O4, a molecular weight of 427.54 g/mole, and the following structural formula:

Ranolazine is a white to off-white solid. Ranolazine is soluble in dichloromethane and methanol; sparingly soluble in tetrahydrofuran, ethanol, acetonitrile, and acetone; slightly soluble in ethyl acetate, isopropanol, toluene, and ethyl ether; and very slightly soluble in water.

RANEXA tablets contain 500 mg or 1000 mg of ranolazine and the following inactive ingredients: carnauba wax, hypromellose, magnesium stearate, methacrylic acid copolymer (Type C), microcrystalline cellulose, polyethylene glycol, sodium hydroxide, and titanium dioxide. Additional inactive ingredients for the 500 mg tablet include polyvinyl alcohol, talc, Iron Oxide Yellow, and Iron Oxide Red; additional inactive ingredients for the 1000 mg tablet include lactose monohydrate, triacetin, and Iron Oxide Yellow.

12 CLINICAL PHARMACOLOGY

12.1 Mechanism of Action

The mechanism of action of ranolazine's antianginal effects has not been determined. Ranolazine has anti-ischemic and antianginal effects that do not depend upon reductions in heart rate or blood pressure. It does not affect the rate-pressure product, a measure of myocardial work, at maximal exercise. Ranolazine at therapeutic levels can inhibit the cardiac late sodium current (INa). However, the relationship of this inhibition to angina symptoms is uncertain.

The QT prolongation effect of ranolazine on the surface electrocardiogram is the result of inhibition of IKr, which prolongs the ventricular action potential.

12.2 Pharmacodynamics

Hemodynamic Effects

Patients with chronic angina treated with RANEXA in controlled clinical studies had minimal changes in mean heart rate (< 2 bpm) and systolic blood pressure (< 3 mm Hg). Similar results were observed in subgroups of patients with CHF NYHA Class I or II, diabetes, or reactive airway disease, and in elderly patients.

Electrocardiographic Effects

Dose and plasma concentration-related increases in the QTc interval [see Warnings and Precautions (5.1)], reductions in T wave amplitude, and, in some cases, notched T waves, have been observed in patients treated with RANEXA. These effects are believed to be caused by ranolazine and not by its metabolites. The relationship between the change in QTc and ranolazine plasma concentrations is linear, with a slope of about 2.6 msec/1000 ng/mL, through exposures corresponding to doses several-fold higher than the maximum recommended dose of 1000 mg twice daily. The variable blood levels attained after a given dose of ranolazine give a wide range of effects on QTc. At Tmax following repeat dosing at 1000 mg twice daily, the mean change in QTc is about 6 msec, but in the 5% of the population with the highest plasma concentrations, the prolongation of QTc is at least 15 msec. In cirrhotic subjects with mild or moderate hepatic impairment, the relationship between plasma level of ranolazine and QTc is much steeper [see Contraindications (4)].

Age, weight, gender, race, heart rate, congestive heart failure, diabetes, and renal impairment did not alter the slope of the QTc-concentration relationship of ranolazine.

No proarrhythmic effects were observed on 7-day Holter recordings in 3162 acute coronary syndrome patients treated with RANEXA. There was a significantly lower incidence of arrhythmias (ventricular tachycardia, bradycardia, supraventricular tachycardia, and new atrial fibrillation) in patients treated with RANEXA (80%) versus placebo (87%), including ventricular tachycardia ≥ 3 beats (52% versus 61%). However, this difference in arrhythmias did not lead to a reduction in mortality, a reduction in arrhythmia hospitalization, or a reduction in arrhythmia symptoms.

12.3 Pharmacokinetics

Ranolazine is extensively metabolized in the gut and liver and its absorption is highly variable. For example, at a dose of 1000 mg twice daily, the mean steady-state Cmax was 2600 ng/mL with 95% confidence limits of 400 and 6100 ng/mL. The pharmacokinetics of the (+) R- and (-) S-enantiomers of ranolazine are similar in healthy volunteers. The apparent terminal half-life of ranolazine is 7 hours. Steady state is generally achieved within 3 days of twice-daily dosing with RANEXA. At steady state over the dose range of 500 to 1000 mg twice daily, Cmax and AUC0–τ increase slightly more than proportionally to dose, 2.2- and 2.4-fold, respectively. With twice-daily dosing, the trough:peak ratio of the ranolazine plasma concentration is 0.3 to 0.6. The pharmacokinetics of ranolazine is unaffected by age, gender, or food.

Absorption and Distribution

After oral administration of RANEXA, peak plasma concentrations of ranolazine are reached between 2 and 5 hours. After oral administration of ^14C-ranolazine as a solution, 73% of the dose is systemically available as ranolazine or metabolites. The bioavailability of ranolazine from RANEXA tablets relative to that from a solution of ranolazine is 76%. Because ranolazine is a substrate of P-gp, inhibitors of P-gp may increase the absorption of ranolazine.

Food (high-fat breakfast) has no important effect on the Cmax and AUC of ranolazine. Therefore, RANEXA may be taken without regard to meals. Over the concentration range of 0.25 to 10 µg/mL, ranolazine is approximately 62% bound to human plasma proteins.

Metabolism and Excretion

Ranolazine is metabolized mainly by CYP3A and, to a lesser extent, by CYP2D6. Following a single oral dose of ranolazine solution, approximately 75% of the dose is excreted in urine and 25% in feces. Ranolazine is metabolized rapidly and extensively in the liver and intestine; less than 5% is excreted unchanged in urine and feces. The pharmacologic activity of the metabolites has not been well characterized. After dosing to steady state with 500 mg to 1500 mg twice daily, the four most abundant metabolites in plasma have AUC values ranging from about 5 to 33% that of ranolazine, and display apparent half-lives ranging from 6 to 22 hours.

Drug Interactions

Effect of Other Drugs on Ranolazine

In vitro data indicate that ranolazine is a substrate of CYP3A and, to a lesser degree, of CYP2D6. Ranolazine is also a substrate of P-glycoprotein.

Strong CYP3A Inhibitors

Plasma levels of ranolazine with RANEXA 1000 mg twice daily are increased by 220% when co-administered with ketoconazole 200 mg twice daily [see Contraindications (4)].

Moderate CYP3A Inhibitors

Plasma levels of ranolazine with RANEXA 1000 mg twice daily are increased by 50 to 130% by diltiazem 180 to 360 mg, respectively. Plasma levels of ranolazine with RANEXA 750 mg twice daily are increased by 100% by verapamil 120 mg three times daily [see Drug Interactions (7.1)].

Weak CYP3A Inhibitors

The weak CYP3A inhibitors simvastatin (20 mg once daily) and cimetidine (400 mg three times daily) do not increase the exposure to ranolazine in healthy volunteers.

CYP3A Inducers

Rifampin 600 mg once daily decreases the plasma concentrations of ranolazine (1000 mg twice daily) by approximately 95% [see Contraindications (4)].

CYP2D6 Inhibitors

Paroxetine 20 mg once daily increased ranolazine concentrations by 20% in healthy volunteers receiving RANEXA 1000 mg twice daily. No dose adjustment of RANEXA is required in patients treated with CYP2D6 inhibitors.

Digoxin

Plasma concentrations of ranolazine are not significantly altered by concomitant digoxin at 0.125 mg once daily.

Effect of Ranolazine on Other Drugs

In vitro ranolazine and its O-demethylated metabolite are weak inhibitors of CYP3A and moderate inhibitors of CYP2D6 and P-gp. In vitro ranolazine is an inhibitor of OCT2.

CYP3A Substrates

The plasma levels of simvastatin, a CYP3A substrate, and its active metabolite are increased by 100% in healthy volunteers receiving 80 mg once daily and RANEXA 1000 mg twice daily [see Drug Interactions (7.2)]. Mean exposure to atorvastatin (80 mg daily) is increased by 40% following co-administration with RANEXA (1000 mg twice daily) in healthy volunteers. However, in one subject the exposure to atorvastatin and metabolites was increased by ~400% in the presence of RANEXA.

Diltiazem

The pharmacokinetics of diltiazem is not affected by ranolazine in healthy volunteers receiving diltiazem 60 mg three times daily and RANEXA 1000 mg twice daily.

P-gp Substrates

Ranolazine increases digoxin concentrations by 50% in healthy volunteers receiving RANEXA 1000 mg twice daily and digoxin 0.125 mg once daily [see Drug Interactions (7.2)].

CYP2D6 Substrates

RANEXA 750 mg twice daily increases the plasma concentrations of a single dose of immediate release metoprolol (100 mg), a CYP2D6 substrate, by 80% in extensive CYP2D6 metabolizers with no need for dose adjustment of metoprolol. In extensive metabolizers of dextromethorphan, a substrate of CYP2D6, ranolazine inhibits partially the formation of the main metabolite dextrorphan.

OCT2 Substrates

In subjects with type 2 diabetes mellitus, the exposure to metformin is increased by 40% and 80% following administration of ranolazine 500 mg twice daily and 1000 mg twice daily, respectively. If co-administered with RANEXA 1000 mg twice daily, do not exceed metformin doses of 1700 mg/day [see Drug Interactions (7.2)].

13 NONCLINICAL TOXICOLOGY

13.1 Carcinogenesis, Mutagenesis, Impairment of Fertility

Ranolazine tested negative for genotoxic potential in the following assays: Ames bacterial mutation assay, Saccharomyces assay for mitotic gene conversion, chromosomal aberrations assay in Chinese hamster ovary (CHO) cells, mammalian CHO/HGPRT gene mutation assay, and mouse and rat bone marrow micronucleus assays.

There was no evidence of carcinogenic potential in mice or rats. The highest oral doses used in the carcinogenicity studies were 150 mg/kg/day for 21 months in rats (900 mg/m^2/day) and 50 mg/kg/day for 24 months in mice (150 mg/m^2/day). These maximally tolerated doses are 0.8 and 0.1 times, respectively, the daily maximum recommended human dose (MRHD) of 2000 mg on a surface area basis. A published study reported that ranolazine promoted tumor formation and progression to malignancy when given to transgenic APC (min/+) mice at a dose of 30 mg/kg twice daily [see References (15)]. The clinical significance of this finding is unclear.

In male and female rats, oral administration of ranolazine that produced exposures (AUC) approximatelty 3-fold or 5-fold higher, respectively, than the MRHD had no effect on fertility.

14 CLINICAL STUDIES

14.1 Chronic Stable Angina

CARISA (Combination Assessment of Ranolazine In Stable Angina) was a study in 823 chronic angina patients randomized to receive 12 weeks of treatment with twice-daily RANEXA 750 mg, 1000 mg, or placebo, who also continued on daily doses of atenolol 50 mg, amlodipine 5 mg, or diltiazem CD 180 mg. Sublingual nitrates were used in this study as needed.

In this trial, statistically significant (p < 0.05) increases in modified Bruce treadmill exercise duration and time to angina were observed for each RANEXA dose versus placebo, at both trough (12 hours after dosing) and peak (4 hours after dosing) plasma levels, with minimal effects on blood pressure and heart rate. The changes versus placebo in exercise parameters are presented in Table 1. Exercise treadmill results showed no increase in effect on exercise at the 1000 mg dose compared to the 750 mg dose.

Table 1 Exercise Treadmill Results (CARISA)
 | Mean Difference from Placebo (sec)
Study | CARISA (N=791)
RANEXA Twice-daily Dose | 750 mg | 1000 mg
Exercise Duration
Trough | 24 [p-value ≤ 0.05] | 24
Peak | 34 [p-value ≤ 0.005] | 26
Time to Angina
Trough | 30 | 26
Peak | 38 | 38
Time to 1 mm ST-Segment Depression
Trough | 20 | 21
Peak | 41 | 35

The effects of RANEXA on angina frequency and nitroglycerin use are shown in Table 2.

Table 2 Angina Frequency and Nitroglycerin Use (CARISA)
 |  | Placebo | RANEXA 750 mg [Twice daily] | RANEXA 1000 mg
Angina Frequency (attacks/week) | N | 258 | 272 | 261
Angina Frequency (attacks/week) | Mean | 3.3 | 2.5 | 2.1
Angina Frequency (attacks/week) | P-value vs placebo | — | 0.006 | < 0.001
Nitroglycerin Use (doses/week) | N | 252 | 262 | 244
Nitroglycerin Use (doses/week) | Mean | 3.1 | 2.1 | 1.8
Nitroglycerin Use (doses/week) | P-value vs placebo | — | 0.016 | < 0.001

Tolerance to RANEXA did not develop after 12 weeks of therapy. Rebound increases in angina, as measured by exercise duration, have not been observed following abrupt discontinuation of RANEXA.

RANEXA has been evaluated in patients with chronic angina who remained symptomatic despite treatment with the maximum dose of an antianginal agent. In the ERICA (Efficacy of Ranolazine In Chronic Angina) trial, 565 patients were randomized to receive an initial dose of RANEXA 500 mg twice daily or placebo for 1 week, followed by 6 weeks of treatment with RANEXA 1000 mg twice daily or placebo, in addition to concomitant treatment with amlodipine 10 mg once daily. In addition, 45% of the study population also received long-acting nitrates. Sublingual nitrates were used as needed to treat angina episodes. Results are shown in Table 3. Statistically significant decreases in angina attack frequency (p=0.028) and nitroglycerin use (p=0.014) were observed with RANEXA compared to placebo. These treatment effects appeared consistent across age and use of long-acting nitrates.

Table 3 Angina Frequency and Nitroglycerin Use (ERICA)
 |  | Placebo | RANEXA [1000 mg twice daily]
Angina Frequency (attacks/week) | N | 281 | 277
Angina Frequency (attacks/week) | Mean | 4.3 | 3.3
Angina Frequency (attacks/week) | Median | 2.4 | 2.2
Nitroglycerin Use (doses/week) | N | 281 | 277
Nitroglycerin Use (doses/week) | Mean | 3.6 | 2.7
Nitroglycerin Use (doses/week) | Median | 1.7 | 1.3

Gender

Effects on angina frequency and exercise tolerance were considerably smaller in women than in men. In CARISA, the improvement in Exercise Tolerance Test (ETT) in females was about 33% of that in males at the 1000 mg twice-daily dose level. In ERICA, where the primary endpoint was angina attack frequency, the mean reduction in weekly angina attacks was 0.3 for females and 1.3 for males.

Race

There were insufficient numbers of non-Caucasian patients to allow for analyses of efficacy or safety by racial subgroup.

14.2 Lack of Benefit in Acute Coronary Syndrome

In a large (n=6560) placebo-controlled trial (MERLIN-TIMI 36) in patients with acute coronary syndrome, there was no benefit shown on outcome measures. However, the study is somewhat reassuring regarding proarrhythmic risks, as ventricular arrhythmias were less common on ranolazine [see Clinical Pharmacology (12.2)], and there was no difference between RANEXA and placebo in the risk of all-cause mortality (relative risk ranolazine:placebo 0.99 with an upper 95% confidence limit of 1.22).

15 REFERENCES

M.A. Suckow et al. The anti-ischemia agent ranolazine promotes the development of intestinal tumors in APC (min/+) mice. Cancer Letters 209(2004):165−9.

HOW SUPPLIED

Product: 68151-5004

NDC: 68151-5004-1 1 TABLET, FILM COATED, EXTENDED RELEASE in a PACKAGE

17 PATIENT COUNSELING INFORMATION

Advise the patient to read the FDA-approved patient labeling (Patient Information).

Inform patients that RANEXA will not abate an acute angina episode.

Strong CY3PA Inhibitors, CYP3A Inducers, Liver Cirrhosis

- Inform patients that RANEXA should not be used with drugs that are strong CYP3A inhibitors (e.g., ketoconazole, clarithromycin, nefazodone, ritonavir) [(see Contraindications (4), Drug Interactions (7.1)].
- Inform patients that RANEXA should not be used with drugs that are inducers of CYP3A (e.g., rifampin, rifabutin, rifapentine, barbiturates, carbamazepine, phenytoin, St. John's wort) [(see Contraindications (4), Drug Interactions (7.1)].
- Inform patients that RANEXA should not be used in patients with liver cirrhosis [(see Contraindications (4), Use in Specific Populations (8.6)].

Moderate CYP3A Inhibitors, P-gp Inhibitors, Grapefruit Products

- Advise patients to inform their physician if they are receiving drugs that are moderate CYP3A inhibitors (e.g., diltiazem, verapamil, erythromycin) [see Drug Interactions (7)].
- Advise patients to inform their physician if they are receiving drugs that are P-gp inhibitors (e.g., cyclosporine) [see Drug Interactions (7)].
- Advise patients to limit grapefruit juice or grapefruit products when taking RANEXA [see Drug Interactions (7)].

QT Interval Prolongation

- Inform patients that RANEXA may produce changes in the electrocardiogram (QTc interval prolongation) [see Warnings and Precautions (5.1)].
- Advise patients to inform their physician of any personal or family history of QTc prolongation, congenital long QT syndrome, or if they are receiving drugs that prolong the QTc interval such as Class Ia (e.g., quinidine) or Class III (e.g., dofetilide, sotalol, amiodarone) antiarrhythmic agents, erythromycin, and certain antipsychotics (e.g., thioridazine, ziprasidone) [see Warnings and Precautions (5.1)].

Use in Patients with Renal Impairment

Patients with severe renal impairment may be at risk of renal failure while on RANEXA. Advise patients to inform their physician if they have impaired renal function before or while taking RANEXA [see Warnings and Precautions (5.2)].

Dizziness, Fainting

- Inform patients that RANEXA may cause dizziness and lightheadedness. Patients should know how they react to RANEXA before they operate an automobile or machinery, or engage in activities requiring mental alertness or coordination [see Adverse Reactions (6.1)].
- Advise patients to contact their physician if they experience fainting spells while taking RANEXA.

Administration

- Instruct patients to swallow RANEXA tablets whole, with or without meals, and not to crush, break, or chew tablets. Inform patients that if a dose is missed, to take the usual dose at the next scheduled time. The next dose should not be doubled. Inform patients that doses of RANEXA higher than 1000 mg twice daily should not be used [see Dosage and Administration (2)].
- Advise patients to inform their physician of any other medications taken concurrently with RANEXA, including over-the-counter medications.

Manufactured for:
Gilead Sciences, Inc.
Foster City, CA 94404

RANEXA is a registered trademark of Gilead Sciences, Inc.
© 2016 Gilead Sciences, Inc.

21-526-GS-015

Patient Information
RANEXA® (rah NEX ah)
(ranolazine)
extended-release tablets
Dosing Strengths:
500 mg tablets
1000 mg tablets

Read this Patient Information before you start taking RANEXA and each time you get a refill. There may be new information. This information does not take the place of talking with your doctor about your medical condition or treatment.

What is RANEXA?

RANEXA is a prescription medicine used to treat angina that keeps coming back (chronic angina).

RANEXA may be used with other medicines that are used for heart problems and blood pressure control.

It is not known if RANEXA is safe and effective in children.

Who should not take RANEXA?

Do not take RANEXA if:

- you take any of the following medicines:
  - for fungus infection: ketoconazole (Nizoral®), itraconazole (Sporanox®, Onmel™)
  - for infection: clarithromycin (Biaxin®)
  - for depression: nefazodone
  - for HIV: nelfinavir (Viracept®), ritonavir (Norvir®), lopinavir and ritonavir (Kaletra®), indinavir (Crixivan®), saquinavir (Invirase®)
  - for tuberculosis (TB): rifampin (Rifadin®), rifabutin (Mycobutin®), rifapentine (Priftin®)
  - for seizures: phenobarbital, phenytoin (Phenytek®, Dilantin®, Dilantin-125®), carbamazepine (Tegretol®)
  - St. John's wort (Hypericum perforatum)
- you have scarring (cirrhosis) of your liver

What should I tell my doctor before taking RANEXA?

Before you take RANEXA, tell your doctor if you:

- have or have a family history of a heart problem, called 'QT prolongation' or 'long QT syndrome'.
- have liver problems.
- have kidney problems.
- are pregnant or plan to become pregnant. It is not known if RANEXA will harm your unborn baby.
- are breast-feeding or plan to breast-feed. It is not known if RANEXA passes into your breast milk. You and your doctor should decide if you will breast-feed.

Tell your doctor about all the medicines you take, including all prescription and nonprescription medicines, vitamins, and herbal supplements. RANEXA may affect the way other medicines work and other medicines may affect how RANEXA works.

Tell your doctor if you take medicines:

- for your heart
- for cholesterol
- for diabetes
- for infection
- for fungus
- for transplant
- for nausea and vomiting because of cancer treatments
- for mental problems

Know the medicines you take. Keep a list of them to show your doctor or pharmacist when you get a new medicine.

How should I take RANEXA?

- Take RANEXA exactly as your doctor tells you.
- Your doctor will tell you how much RANEXA to take and when to take it.
- Do not change your dose unless your doctor tells you to.
- Tell your doctor if you still have symptoms of angina after starting RANEXA.
- Take RANEXA by mouth, with or without food.
- Swallow the RANEXA tablets whole. Do not crush, break, or chew RANEXA tablets before swallowing.
- If you miss a dose of RANEXA, wait to take the next dose of RANEXA at your regular time. Do not make up for the missed dose. Do not take more than 1 dose at a time.
- If you take too much RANEXA, call your doctor, or go to the nearest emergency room right away.

What should I avoid while taking RANEXA?

- Grapefruit and grapefruit juice. Limit products that have grapefruit in them. They can cause your blood levels of RANEXA to increase.
- RANEXA can cause dizziness, lightheadedness, or fainting. If you have these symptoms, do not drive a car, use machinery, or do anything that needs you to be alert.

What are the possible side effects of RANEXA?

RANEXA may cause serious side effects, including:

- changes in the electrical activity of your heart called QT prolongation. Your doctor may check the electrical activity of your heart with an ECG. Tell your doctor right away if you feel faint, lightheaded, or feel your heart beating irregularly or fast while taking RANEXA. These may be symptoms related to QT prolongation.
- kidney failure in people who already have severe kidney problems. Your doctor may need to do tests to check how your kidneys are working.

The most common side effects of RANEXA include:

- dizziness
- headache
- constipation
- nausea

Tell your doctor if you have any side effect that bothers you or does not go away.

These are not all the possible side effects of RANEXA. For more information, ask your doctor or pharmacist.

Call your doctor for medical advice about side effects. You may report side effects to FDA at 1-800-FDA-1088.

How should I store RANEXA?

Store RANEXA tablets at room temperature between 59° to 86°F (15° to 30°C).

Keep RANEXA and all medicines out of the reach of children.

General information about RANEXA.

Medicines are sometimes prescribed for purposes other than those listed in the Patient Information. Do not use RANEXA for a condition for which it was not prescribed. Do not give RANEXA to other people, even if they have the same condition you have. It may harm them.

The Patient Information summarizes the most important information about RANEXA. If you would like more information, talk with your doctor. You can ask your pharmacist or doctor for information about RANEXA that is written for health professionals.

For more information, go to www.ranexa.com or call Gilead Sciences, Inc. at 1-800-445-3235.

What is chronic angina?

Chronic angina means pain or discomfort in the chest, jaw, shoulder, back, or arm that keeps coming back. There are other possible signs and symptoms of angina including shortness of breath. Angina usually comes on when you are active or under stress. Chronic angina is a symptom of a heart problem called coronary heart disease (CHD), also known as coronary artery disease (CAD). When you have CHD, the blood vessels in your heart become stiff and narrow. Oxygen-rich blood cannot reach your heart muscle easily. Angina comes on when too little oxygen reaches your heart muscle.

What are the ingredients in RANEXA?

Active ingredient: ranolazine

Inactive ingredients:
500 mg tablet: carnauba wax, hypromellose, magnesium stearate, methacrylic acid copolymer (Type C), microcrystalline cellulose, polyethylene glycol, sodium hydroxide, titanium dioxide, polyvinyl alcohol, talc, Iron Oxide Yellow, and Iron Oxide Red.
1000 mg tablet: carnauba wax, hypromellose, magnesium stearate, methacrylic acid copolymer (Type C), microcrystalline cellulose, polyethylene glycol, sodium hydroxide, titanium dioxide, lactose monohydrate, triacetin, and Iron Oxide Yellow.

This Patient Information has been approved by the U.S. Food and Drug Administration.

Manufactured for:
Gilead Sciences, Inc.
Foster City, CA 94404

Revised: January 2016

RANEXA is a trademark of Gilead Sciences, Inc., or its related companies. All other trademarks referenced herein are the property of their respective owners.

© 2016 Gilead Sciences, Inc.

21-526-GS-015